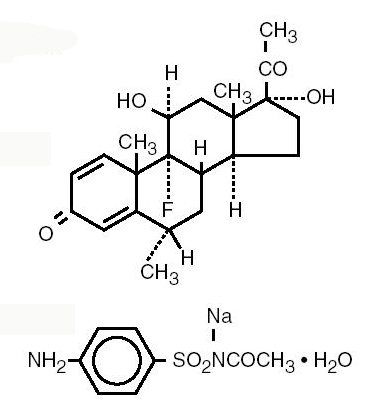 DRUG LABEL: Unknown
Manufacturer: Allergan, Inc.
Category: prescription | Type: HUMAN PRESCRIPTION DRUG LABELING
Date: 20070220

FML-S®
(fluorometholone and sulfacetamide sodium ophthalmic suspension, USP) 0.1%/10%

Sterile

DESCRIPTION

FML-S® ophthalmic suspension is a topical anti-inflammatory/anti-infective product for ophthalmic use.

Chemical Names:

Fluorometholone:

9-Fluoro-11β,17-dihydroxy-6α–methylpregna-1,4-diene-3,20-dione.

Sulfacetamide sodium:

N-Sulfanilyacetamide monosodium salt monohydrate.

Structural Formulas:

Contains: Actives: fluorometholone 0.1%; and sulfacetamide sodium 10%. Preservative: benzalkonium chloride 0.006%. Inactives: edetate disodium; polysorbate 80; polyvinyl alcohol (1.4%); povidone; purified water; sodium chloride; sodium phosphate dibasic; sodium phosphate, monobasic; sodium thiosulfate; and hydrochloric acid and/or sodium hydroxide to adjust the pH to 7.0 to 7.5.

CLINICAL PHARMACOLOGY

Corticosteroids suppress the inflammatory response to a variety of agents and they probably delay or slow healing. They inhibit the edema, fibrin deposition, capillary dilation, leukocyte migration, capillary proliferation, fibroblast proliferation, deposition of collagen, and scar formation associated with inflammation. Since corticosteroids may inhibit the body's defense mechanism against infection, a concomitant antimicrobial drug may be used when this inhibition is considered to be clinically significant in a particular case.

Corticosteroids are capable of producing a rise in intraocular pressure. In clinical studies of documented steroid-responders, fluorometholone demonstrated a significantly longer average time to produce a rise in intraocular pressure than dexamethasone phosphate; however, in a small percentage of individuals, a significant rise in intraocular pressure occurred within one week. The ultimate magnitude of the rise was equivalent for both drugs.

The anti-infective component in FML-S® ophthalmic suspension is included to provide action against specific organisms susceptible to it. Sulfacetamide sodium is active in vitro against susceptible strains of the following microorganisms: Escherichia coli, Staphylococcus aureus, Streptococcus pneumoniae, Streptococcus (viridans group), Haemophilus influenzae, Klebsiella species, and Enterobacter species. Some strains of these bacteria may be resistant to sulfacetamide or resistant strains may emerge in vivo.

When a decision to administer both a corticosteroid and an antimicrobial is made, the administration of such drugs in combination has the advantage of greater patient compliance and convenience, with the added assurance that the appropriate dosage of both drugs is administered. When both types of drugs are in the same formulation, compatibility of ingredients is assured and the correct volume of drug is delivered and retained.

The relative potency of corticosteroid formulations depends on the molecular structure, concentration, and release from the vehicle.

INDICATIONS AND USAGE

FML-S® ophthalmic suspension is indicated for steroid-responsive inflammatory ocular conditions for which a corticosteroid is indicated and where superficial bacterial ocular infection or a risk of bacterial ocular infection exists.

Ocular steroids are indicated in inflammatory conditions of the palpebral and bulbar conjunctiva, cornea and anterior segment of the globe, where the inherent risk of steroid use in certain infective conjunctivitides is accepted to obtain a diminution in edema and inflammation. They are also indicated in chronic anterior uveitis and corneal injury from chemical, radiation or thermal burns or penetration of foreign bodies.

The use of a combination drug with an anti-infective component is indicated where the risk of superficial ocular infection is high or where there is an expectation that potentially dangerous numbers of bacteria will be present in the eye.

The anti-infective drug in this product, sulfacetamide, is active against the following common bacterial eye pathogens: Escherichia coli, Staphylococcus aureus, Streptococcus pneumoniae, Streptococcus (viridans group), Haemophilus influenzae, Klebsiella species, and Enterobacter species.

This product does not provide adequate coverage against Neisseria species and Serratia marcescens. A significant percentage of staphylococcal isolates are completely resistant to sulfa drugs.

CONTRAINDICATIONS

FML-S® ophthalmic suspension is contraindicated in most viral diseases of the cornea and conjunctiva, including epithelial herpes simplex keratitis (dendritic keratitis), vaccinia and varicella, and also in mycobacterial infection of the eye and fungal diseases of ocular structures. FML-S® ophthalmic suspension is also contraindicated in individuals with known or suspected hypersensitivity to any of the ingredients of this preparation, to sulfonamides and to other corticosteroids.

WARNINGS

Prolonged use of corticosteroids may result in glaucoma, with damage to the optic nerve, defects in visual acuity and fields of vision, and in posterior subcapsular cataract formation. Prolonged use may also suppress the host immune response and thus increase the hazard of secondary ocular infections.

Various ocular diseases and long-term use of topical corticosteroids have been known to cause corneal and scleral thinning. Use of topical corticosteroids in the presence of thin corneal or scleral tissue may lead to perforation.

Acute purulent infections of the eye may be masked or activity enhanced by the presence of corticosteroid medication.

If this product is used for 10 days or longer, intraocular pressure should be routinely monitored even though it may be difficult in children and uncooperative patients. Steroids should be used with caution in the presence of glaucoma. Intraocular pressure should be checked frequently.

The use of steroids after cataract surgery may delay healing and increase the incidence of bleb formation.

Use of ocular steroids may prolong the course and may exacerbate the severity of many viral infections of the eye (including herpes simplex). Employment of a corticosteroid medication in the treatment of patients with a history of herpes simplex requires great caution; frequent slit lamp microscopy is recommended.

FML-S® ophthalmic suspension is not for injection. It should never be injected subconjunctivally, nor should it be directly introduced into the anterior chamber of the eye.

FATALITIES HAVE OCCURRED, ALTHOUGH RARELY, DUE TO SEVERE REACTIONS TO SULFONAMIDES INCLUDING STEVENS-JOHNSON SYNDROME, TOXIC EPIDERMAL NECROLYSIS, FULMINANT HEPATIC NECROSIS, AGRANULOCYTOSIS, APLASTIC ANEMIA AND OTHER BLOOD DYSCRASIAS. Sensitizations may recur when a sulfonamide is readministered, irrespective of the route of administration. If signs of hypersensitivity or other serious reactions occur, discontinue use of this preparation (see ADVERSE REACTIONS).

Cross-sensitivity among corticosteroids has been demonstrated.

A significant percentage of staphylococcal isolates are completely resistant to sulfa drugs.

PRECAUTIONS

General:

The initial prescription and renewal of the medication order beyond 20 milliliters of FML-S® ophthalmic suspension should be made by a physician only after examination of the patient with the aid of magnification, such as slit lamp biomicroscopy and, where appropriate, fluorescein staining. If signs and symptoms fail to improve after two days, the patient should be re-evaluated.

As fungal infections of the cornea are particularly prone to develop coincidentally with long-term local corticosteroid applications, fungal invasion should be suspected in any persistent corneal ulceration where a corticosteroid has been used or is in use. Fungal cultures should be taken when appropriate.

If this product is used for 10 days or longer, intraocular pressure should be monitored (see WARNINGS).

Prolonged use of topical anti-bacterial agents may give rise to overgrowth of nonsusceptible organisms including fungi. Bacterial resistance to sulfonamides may also develop.

The effectiveness of sulfonamides may be reduced by the para-aminobenzoic acid present in purulent exudates.

Information for Patients:

If inflammation or pain persists longer than 48 hours or becomes aggravated, the patient should be advised to discontinue use of the medication and consult a physician.

This product is sterile when packaged. To prevent contamination, care should be taken to avoid touching the bottle tip to eyelids or to any other surface. The use of this bottle by more than one person may spread infection. Keep bottle tightly closed when not in use. Keep out of the reach of children.

Drug Interactions:

Sulfacetamide preparations are incompatible with silver preparations.

Carcinogenesis, mutagenesis, impairment of fertility:

No studies have been conducted in animals or in humans to evaluate the possibility of these effects with fluorometholone or sulfacetamide.

Pregnancy:

Teratogenic effects: Pregnancy Category C:

Animal studies have not been conducted with FML-S® ophthalmic suspension. Fluorometholone has been shown to be embryocidal and teratogenic in rabbits when administered at low multiples of the human dose. Fluorometholone was applied ocularly to rabbits daily on days 6-18 of gestation and dose-related fetal loss and fetal abnormalities including cleft palate, deformed rib cage, anomalous limbs and neural abnormalities such as encephalocele, craniorachischisis, and spina bifida were observed. Kernicterus may be precipitated in infants by sulfonamides being given systemically during the third trimester of pregnancy. There are no adequate and well-controlled studies of FML-S® ophthalmic suspension in pregnant women, and it is not known whether FML-S® ophthalmic suspension can cause fetal harm when administered to a pregnant woman. FML-S® ophthalmic suspension should be used during pregnancy only if the potential benefit justifies the potential risk to the fetus.

Nursing Mothers:

It is not known whether topical administration of corticosteroids could result in sufficient systemic absorption to produce detectable quantities in breast milk. Systemically administered corticosteroids appear in breast milk and could suppress growth, interfere with endogenous corticosteroid production, or cause other untoward effects. Systemically administered sulfonamides are capable of producing kernicterus in infants of lactating women. Because of the potential for serious adverse reactions in nursing infants from FML-S® ophthalmic suspension, a decision should be made whether to discontinue nursing or to discontinue the medication.

Pediatric Use:

Safety and effectiveness in pediatric patients below the age of 2 years have not been established.

Geriatric Use:

No overall differences in safety or effectiveness have been observed between elderly and younger patients.

ADVERSE REACTIONS

Adverse reactions have occurred with corticosteroid/anti-infective combination drugs which can be attributed to the corticosteroid component, the anti-infective component, or the combination. Exact incidence figures are not available, since no denominator of treated patients is available.

Reactions occurring most often from the presence of the anti-infective ingredient are allergic sensitizations. Fatalities have occurred, although rarely, due to severe reactions to sulfonamides including Stevens-Johnson syndrome, toxic epidermal necrolysis, fulminant hepatic necrosis, agranulocytosis, aplastic anemia, and other blood dyscrasias (See WARNINGS). Sulfacetamide sodium may cause local irritation.

The reactions due to the corticosteroid component in decreasing order of frequency are: elevation of intraocular pressure (IOP) with possible development of glaucoma, and infrequent optic nerve damage; posterior subcapsular cataract formation; and delayed wound healing.

Corticosteroid-containing preparations have also been reported to cause perforation of the globe. Keratitis, conjunctivitis, corneal ulcers, and conjunctival hyperemia have occasionally been reported following local use of steroids.

Secondary Infection: The development of secondary infection has occurred after use of combinations containing corticosteroids and antimicrobials. Fungal infections of the cornea are particularly prone to develop coincidentally with long-term applications of corticosteroids. When signs of chronic ocular inflammation persist following prolonged corticosteroid dosing, the possibility of fungal infections of the cornea should be considered.

Secondary bacterial ocular infection following suppression of host responses also occurs.

DOSAGE AND ADMINISTRATION

One drop of FML-S® ophthalmic suspension should be instilled into the conjunctival sac four times daily. Care should be taken not to discontinue therapy prematurely. If signs and symptoms fail to improve after two days, the patient should be re-evaluated (see PRECAUTIONS).

The dosing of FML-S® ophthalmic suspension may be reduced, but care should be taken not to discontinue therapy prematurely. In chronic conditions, withdrawal of treatment should be carried out by gradually decreasing the frequency of applications.

HOW SUPPLIED

FML-S® (fluorometholone and sulfacetamide sodium ophthalmic suspension, USP) 0.1%/10% is supplied sterile in opaque white LDPE plastic bottles with droppers with white high impact polystyrene (HIPS) caps as follows:

5 mL in 10 mL bottle - NDC 11980-422-05
10 mL in 15 mL bottle - NDC 11980-422-10

Note: Store at 15°C - 30°C (59° -86°F). Protect from freezing and light. SHAKE WELL BEFORE USING. Do not use suspension if it is dark brown.

Rx Only

Rev February 2005

© 2005 Allergan, Inc.

® marks owned by Allergan, Inc.
7767X
71745US10P